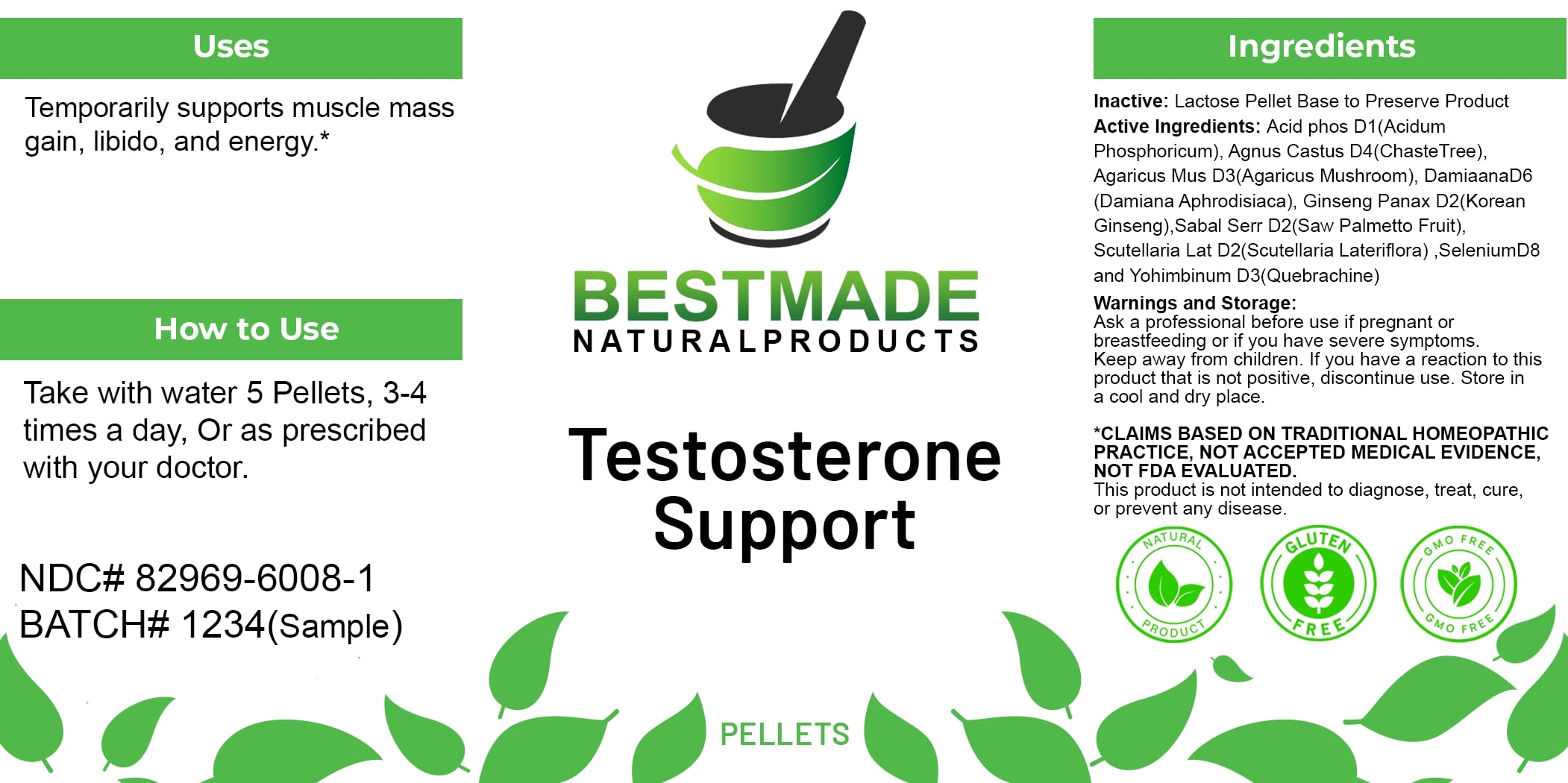 DRUG LABEL: Bestmade Natural Products Testosterone Support
NDC: 82969-6008 | Form: TABLET, SOLUBLE
Manufacturer: Bestmade Natural Products
Category: homeopathic | Type: HUMAN OTC DRUG LABEL
Date: 20250314

ACTIVE INGREDIENTS: AMERICAN GINSENG 30 [hp_C]/30 [hp_C]; PHOSPHORIC ACID 30 [hp_C]/30 [hp_C]; AMANITA MUSCARIA FRUITING BODY 30 [hp_C]/30 [hp_C]; TURNERA DIFFUSA LEAFY TWIG 30 [hp_C]/30 [hp_C]; SAW PALMETTO 30 [hp_C]/30 [hp_C]; SCUTELLARIA LATERIFLORA WHOLE 30 [hp_C]/30 [hp_C]; SELENIUM 30 [hp_C]/30 [hp_C]; YOHIMBINE 30 [hp_C]/30 [hp_C]; CHASTE TREE 30 [hp_C]/30 [hp_C]
INACTIVE INGREDIENTS: LACTOSE 30 [hp_C]/30 [hp_C]

Testosterone Support

DOSAGE AND ADMINISTRATION

How to Use

Take with water 5 Pellets, 3-4 times a day, or as prescribed with your doctor.

Uses

Temporarily supports muscle mass gain, libido, and energy.*

*CLAIMS BASED ON TRADITIONAL HOMEOPATHIC PRACTICE, NOT ACCEPTED MEDICAL EVIDENCE, NOT FDA EVALUATED. This product is not intended to diagnose, treat, cure, or prevent any disease.

Uses

Temporarily supports muscle mass gain, libido, and energy.*

*CLAIMS BASED ON TRADITIONAL HOMEOPATHIC PRACTICE, NOT ACCEPTED MEDICAL EVIDENCE, NOT FDA EVALUATED. This product is not intended to diagnose, treat, cure, or prevent any disease.

INACTIVE INGREDIENT

Ingredients

Inactive: Lactose Pellet Base to Preserve Product

ACTIVE INGREDIENT

Active Ingredients: Acid phos D1(Acidum Phosphoricum), Agnus Castus D4(Chaste Tree), Agaricus Mus D3(Agaricus Mushroom), Damiana D6(Damiana Aphrodisiaca), Ginseng Panax D2(Korean Ginseng), Sabal Serr D2(Saw Palmetto Fruit), Scutellaria Lat D2(Scutellaria Lateriflora), Selenium D8 and Yohimbinum D3(Quebrachine)

KEEP OUT OF REACH OF CHILDREN

Warnings and Storage: Ask a professional before use if pregnant or breastfeeding or if you have severe symptoms. Keep away from children. If you have a reaction to this product that is not positive, discontinue use. Store in a cool and dry place.

WARNINGS

Warnings and Storage: Ask a professional before use if pregnant or breastfeeding or if you have severe symptoms. Keep away from children. If you have a reaction to this product that is not positive, discontinue use. Store in a cool and dry place.

*CLAIMS BASED ON TRADITIONAL HOMEOPATHIC PRACTICE, NOT ACCEPTED MEDICAL EVIDENCE, NOT FDA EVALUATED. This product is not intended to diagnose, treat, cure, or prevent any disease.

Entire package label